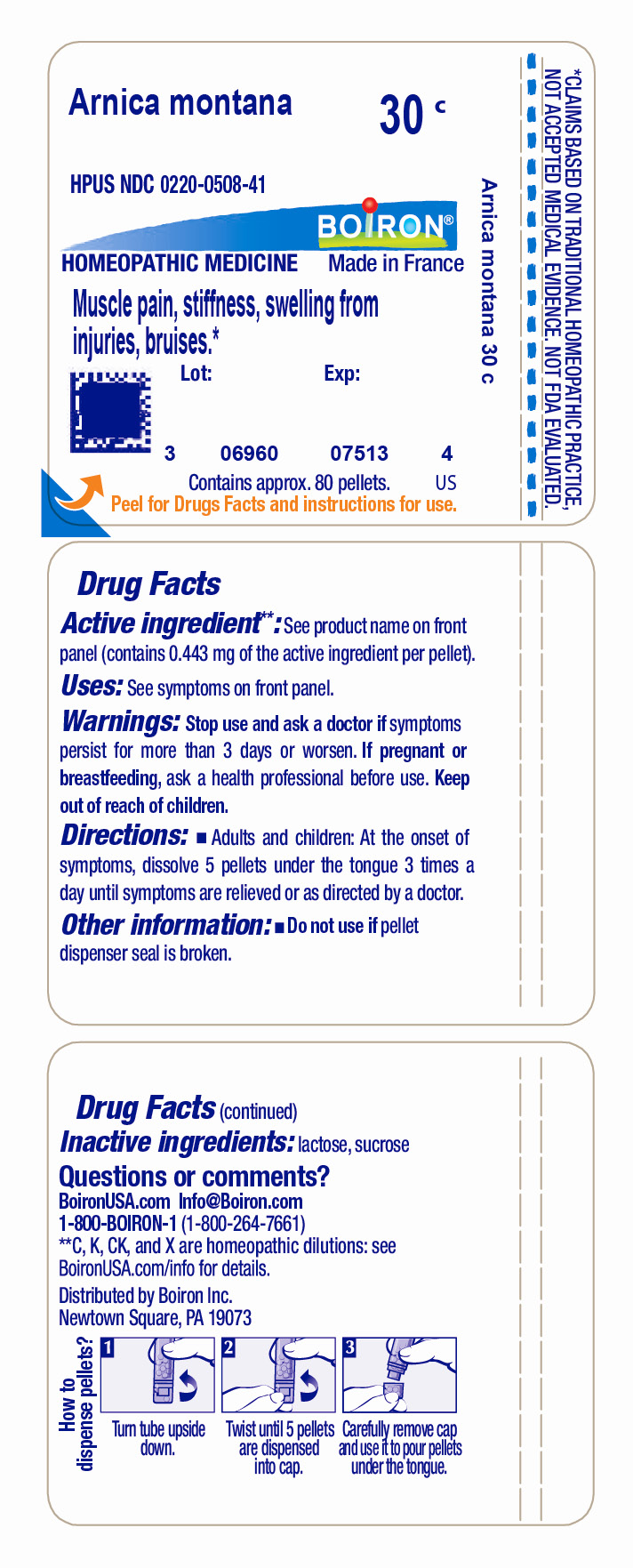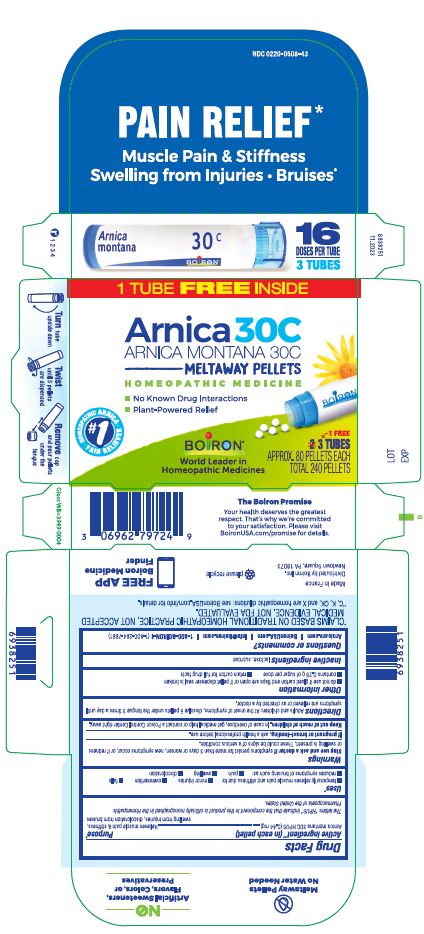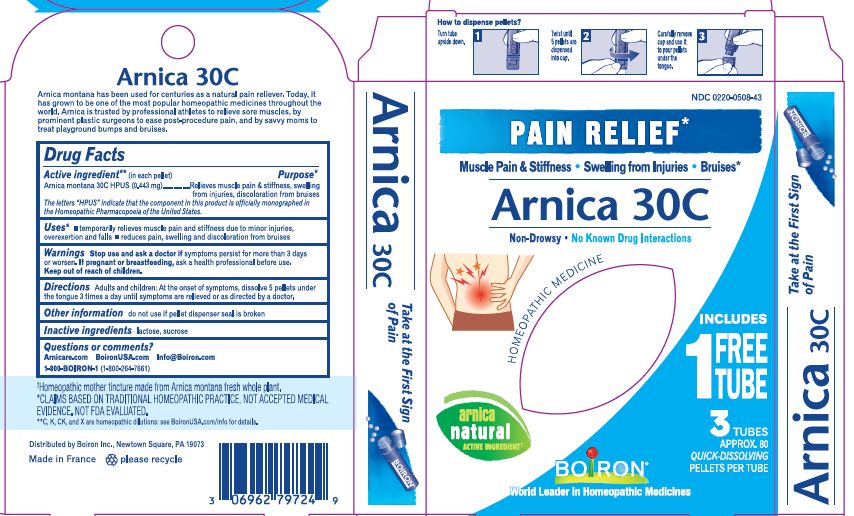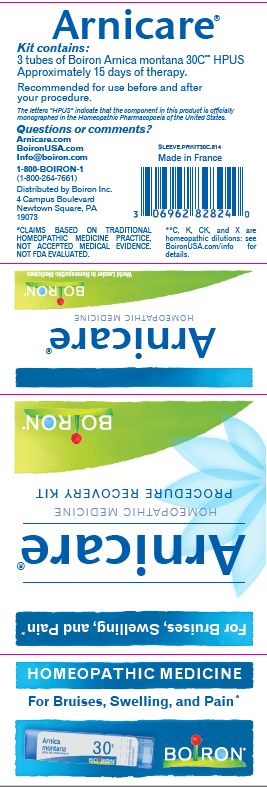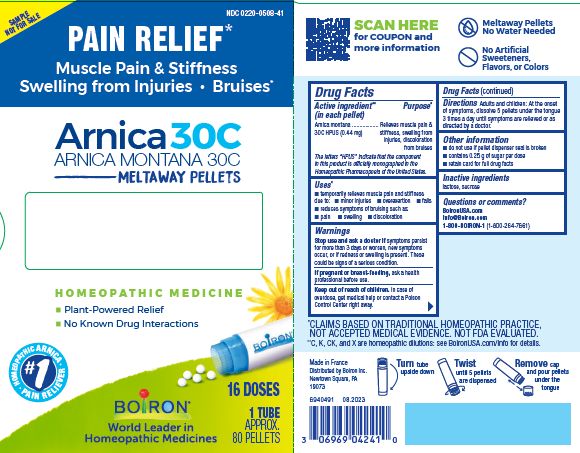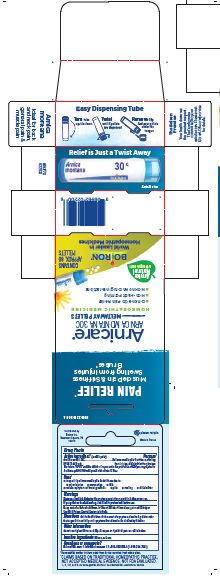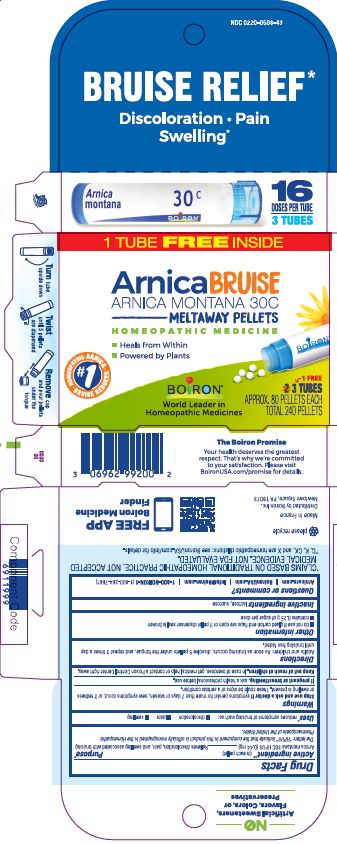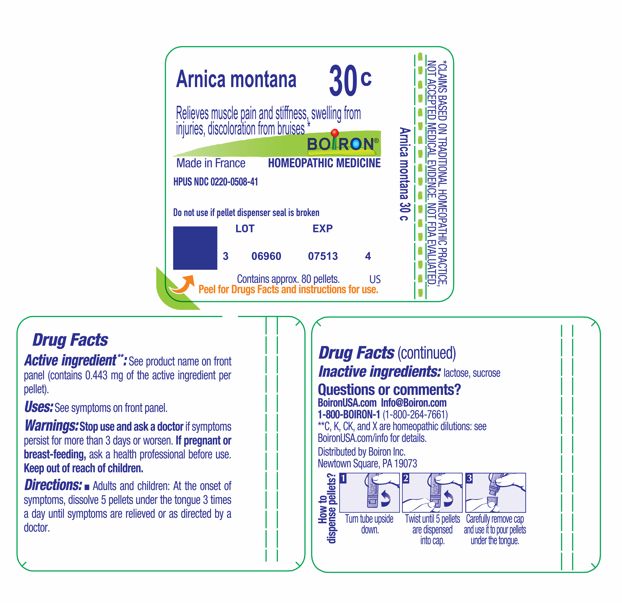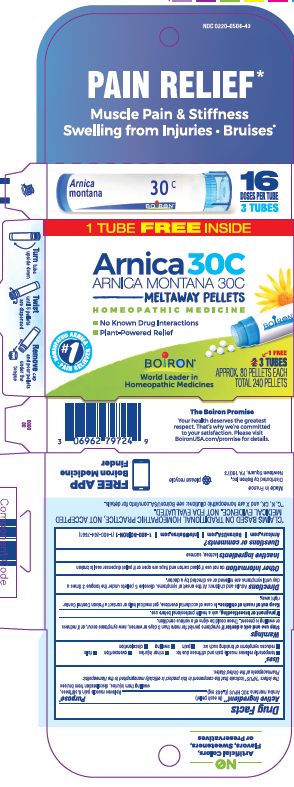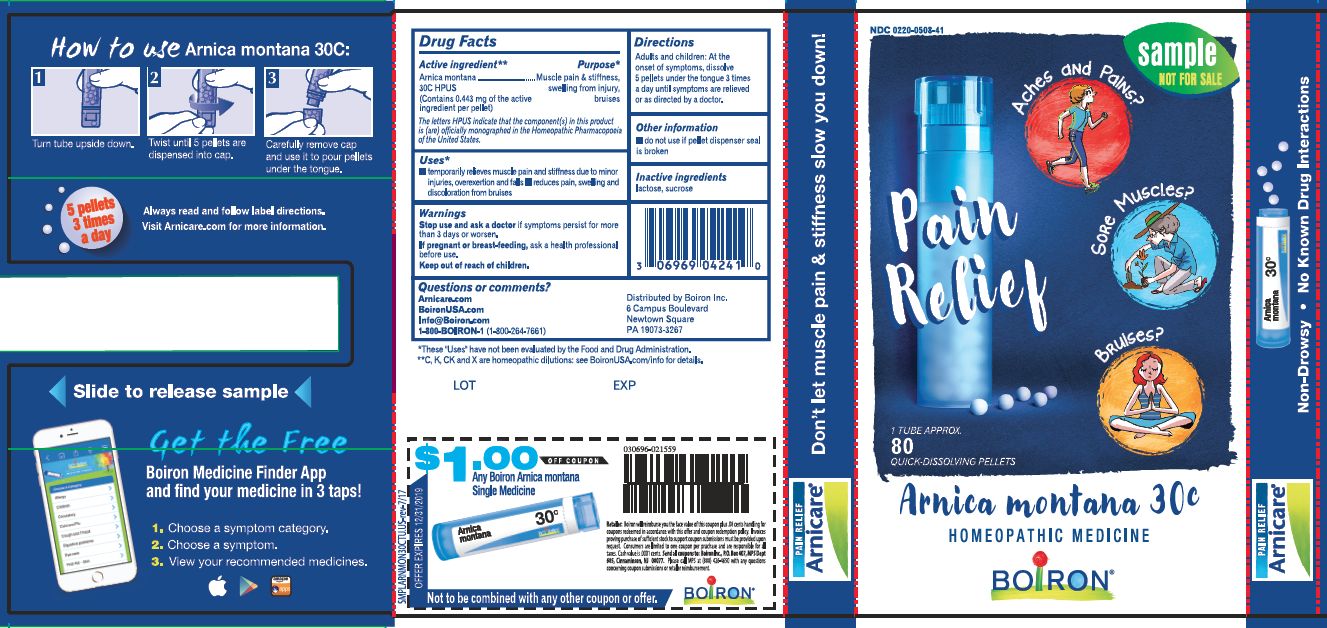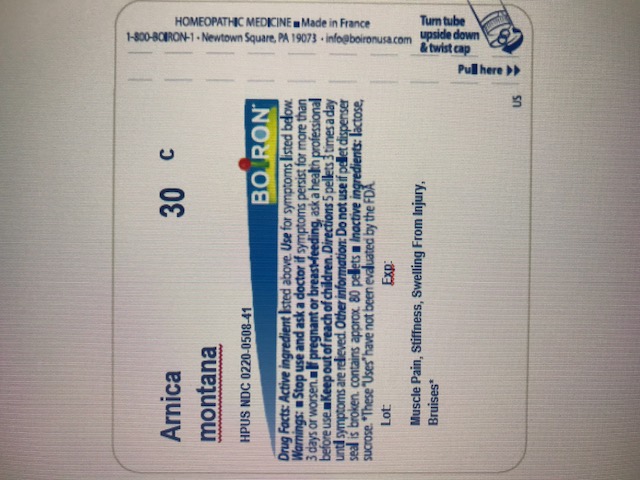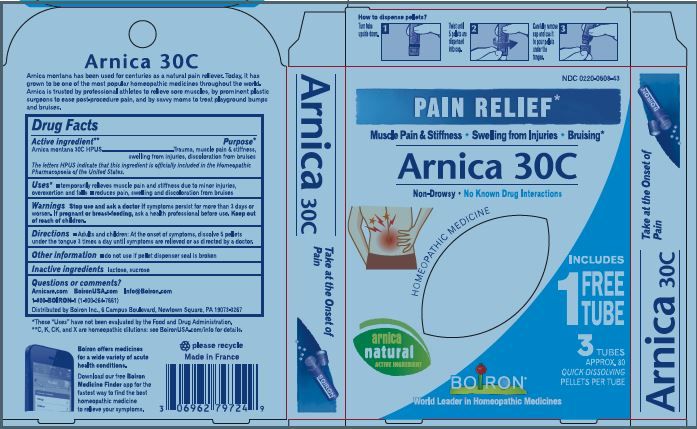 DRUG LABEL: Arnica
NDC: 0220-0508 | Form: PELLET
Manufacturer: Laboratoires Boiron
Category: homeopathic | Type: HUMAN OTC DRUG LABEL
Date: 20251229

ACTIVE INGREDIENTS: ARNICA MONTANA 30 [hp_C]/1 1
INACTIVE INGREDIENTS: SUCROSE; LACTOSE

Arnica montana 30C Bonus Pack

Active ingredient** (in each pellet)

Arnica montana 30C HPUS (0.44 mg)

The letters "HPUS" indicate that the component in this product is officially monographed in Homeopathic Pharmacopoeia of the United States.

Purpose*

Relieves muscle pain & stiffness, swelling from injuries, discoloration from bruises

Relieves discoloration, pain, and swelling with bruising

Uses*

temporarily relieves muscle pain and stiffness due to:

- minor injuries
- overexertion
- falls

reduces symptoms of bruising such as:

- pain
- swelling
- discoloration

Stop use and ask a doctor if symptoms persist for more than 3 days or worsen, new symptoms occur, or if redness or swelling is present. These could be signs of a serious condition.

Stop use and ask a doctor if symptoms persist for more than 7 days or worsen, new symptoms occur, or if redness or swelling is present. These could be signs of a serious condition.

PREGNANCY OR BREAST FEEDING

If pregnant or breast-feeding, ask a health professional before use.

Keep out of reach of children. In case of overdose, get medical help or contact a Poison Control Center right away.

Directions

Adults and children: At the onset of symptoms, dissolve 5 pellets under the tongue 3 times a day until symptoms are relieved or as directed by a doctor.

INACTIVE INGREDIENT

lactose, sucrose.

- do not use if glued carton end flaps are open or if the pellet dispenser seal is broken.
- contains 0.25 g of sugar per dose
- retain carton for full drug facts

Pain Relief"

Muscle Pain & Stiffness, Swelling from Injuries, Bruises*

Bruise Relief*

Discoloration Pain Swelling*

No Known Drug Interactions

How to dispense pellets? Turn tube upside down Twist until 5 pellets are dispensed Remove the cap and pour pellets under the tongue.

16 Doses per Tube

3 Tubes approx. 80 quick dissolving pellets per tube

Total 240 Pellets

*Claims are based on traditional homeopathic practice, not accepted medical evidence. Not FDA evaluated

**C,K,CK, and X are homeopathic dilutions: see BoironUSA.com/info for details.

Questions or Comments?
Arnicare.com

BoironUSA.com

Info@Boiron.com

1-800-BOIRON-1

(1-800-264-7661)

Made in France

Distributed by Boiron Inc.
Newtown Square, PA 19073-3267